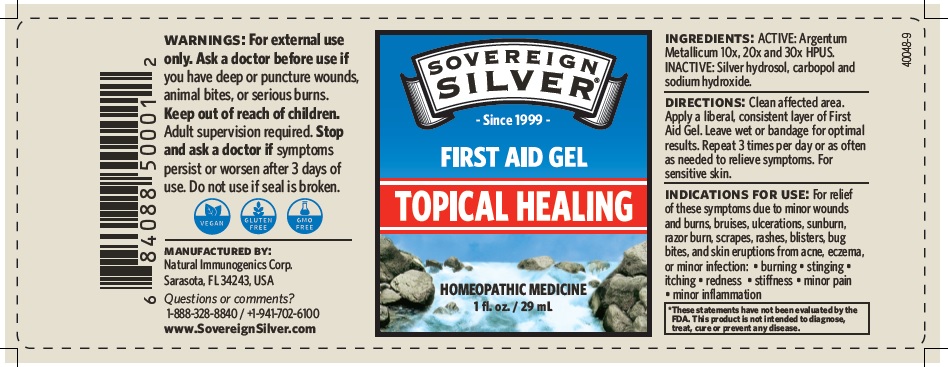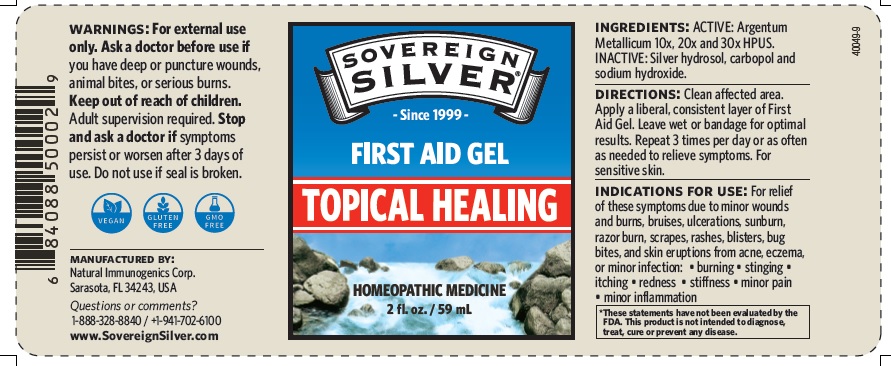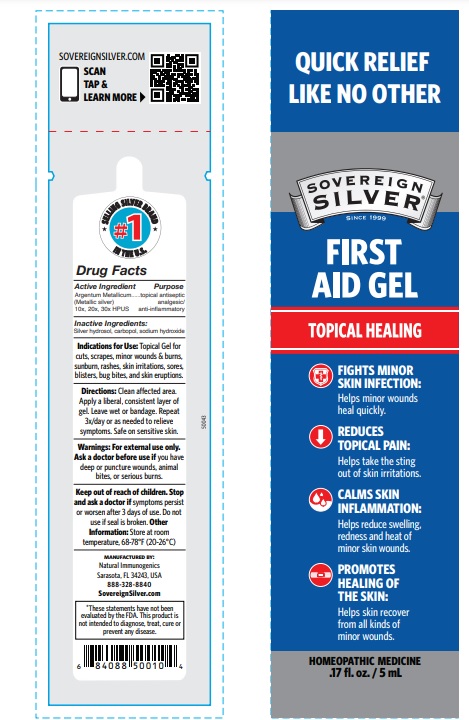 DRUG LABEL: Sovereign Silver

NDC: 52166-002 | Form: GEL
Manufacturer: Natural Immunogenics Corp.dba SOVEREIGN NATURALS
Category: homeopathic | Type: HUMAN OTC DRUG LABEL
Date: 20250522

ACTIVE INGREDIENTS: SILVER 30 [hp_X]/1 mL
INACTIVE INGREDIENTS: CARBOMER HOMOPOLYMER TYPE B (ALLYL PENTAERYTHRITOL CROSSLINKED); SODIUM HYDROXIDE

Homeopathic Drug

Ingredients: ACTIVE:

Argentum Metallicum 10x, 20x and 30x HPUS

INACTIVE: Silver hydrosol,

carbopol and sodium hydroxide

Purpose

First Aid Gel

Homeopathic medicine

Keep out of reach of children.

Adult supervision required

Warnings. For external

use only. Ask a doctor before use if

you have deep or puncture wounds, animal bites or serious burns.

Stop and ask a doctor if

symptoms persist or worsen after 3 days of use. Do not use if

seal is broken

DOSAGE AND ADMINISTRATION

Enter section text here Directions. Clean affected area.

Apply a liberal, consistent layer of First Aid Gel. Leave wet or bandage for

optimal results. Repeat 3 times per day or as often as needed to relieve symptoms.

For sensitive skin.

INDICATIONS AND USAGE

Indications for Use: For relief of these symptoms due to

minor wounds and burns, bruises, ulcerations, sunburn, razor burns,

scrapes, rashes, blisters, bug bites and skin eruptions from acne, eczema

or minor infection:

burning

stinging

itching

redness

stiffness

minor pain

minor inflammation